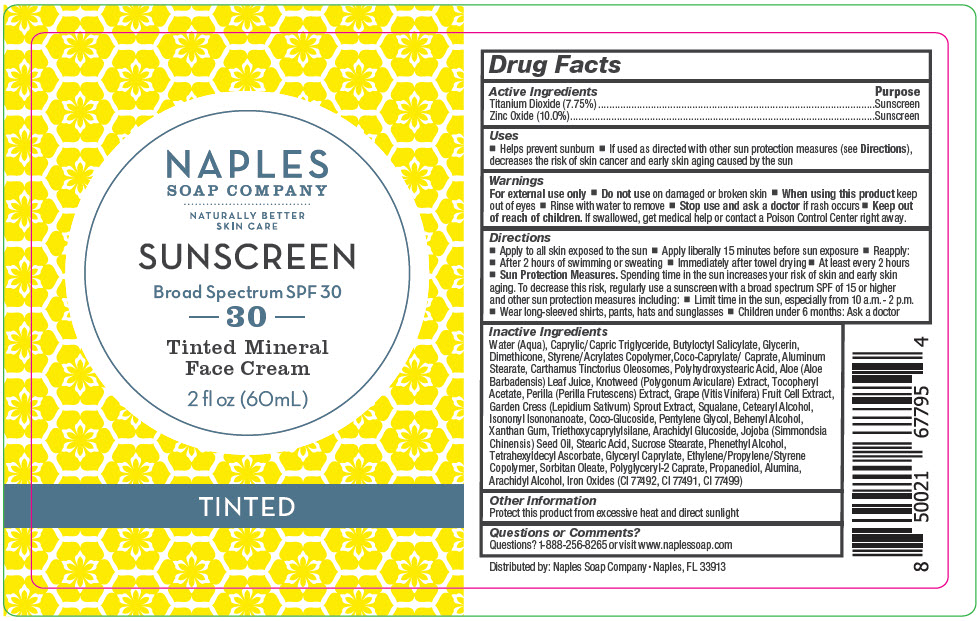 DRUG LABEL: Naples Company - Sunscreen Broad Spectrum SPF 30 Tinted Mineral Face
NDC: 66163-0602 | Form: CREAM
Manufacturer: Cosmetic Solutions LLC
Category: otc | Type: HUMAN OTC DRUG LABEL
Date: 20220607

ACTIVE INGREDIENTS: Titanium Dioxide 7.75 g/100 mL; Zinc Oxide 10 g/100 mL
INACTIVE INGREDIENTS: WATER; MEDIUM-CHAIN TRIGLYCERIDES; BUTYLOCTYL SALICYLATE; GLYCERIN; DIMETHICONE; COCOYL CAPRYLOCAPRATE; ALUMINUM STEARATE; CARTHAMUS TINCTORIUS SEED OLEOSOMES; ALOE VERA LEAF; POLYGONUM AVICULARE TOP; .ALPHA.-TOCOPHEROL ACETATE; GARDEN CRESS SPROUT; SQUALANE; CETOSTEARYL ALCOHOL; ISONONYL ISONONANOATE; COCO GLUCOSIDE; PENTYLENE GLYCOL; DOCOSANOL; XANTHAN GUM; TRIETHOXYCAPRYLYLSILANE; ARACHIDYL GLUCOSIDE; JOJOBA OIL; STEARIC ACID; SUCROSE STEARATE; PHENYLETHYL ALCOHOL; TETRAHEXYLDECYL ASCORBATE; GLYCERYL MONOCAPRYLATE; SORBITAN MONOOLEATE; POLYGLYCERYL-2 CAPRATE; PROPANEDIOL; ALUMINUM OXIDE; ARACHIDYL ALCOHOL; FERRIC OXIDE YELLOW; FERRIC OXIDE RED; FERROSOFERRIC OXIDE

Naples Soap Company - Sunscreen Broad Spectrum SPF 30 Tinted Mineral Face Cream

Drug Facts

ACTIVE INGREDIENT

Active Ingredients | Purpose
Titanium Dioxide (7.75%) | Sunscreen
Zinc Oxide (10.0%) | Sunscreen

Uses

- Helps prevent sunburn
- If used as directed with other sun protection measures (see Directions), decreases the risk of skin cancer and early skin aging caused by the sun

Warnings

For external use only

- Do not use on damaged or broken skin

- When using this product keep out of eyes
- Rinse with water to remove

- Stop use and ask a doctor if rash occurs

- Keep out of reach of children. If swallowed, get medical help or contact a Poison Control Center right away.

Directions

- Apply to all skin exposed to the sun
- Apply liberally 15 minutes before sun exposure
- Reapply:
  - After 2 hours of swimming or sweating
  - Immediately after towel drying
  - At least every 2 hours

- Sun Protection Measures. Spending time in the sun increases your risk of skin and early skin aging. To decrease this risk, regularly use a sunscreen with a broad spectrum SPF of 15 or higher and other sun protection measures including:
  - Limit time in the sun, especially from 10 a.m. - 2 p.m.
  - Wear long-sleeved shirts, pants, hats and sunglasses
  - Children under 6 months: Ask a doctor

Inactive Ingredients

Water (Aqua), Caprylic/Capric Triglyceride, Butyloctyl Salicylate, Glycerin, Dimethicone, Styrene/Acrylates Copolymer,Coco-Caprylate/ Caprate, Aluminum Stearate, Carthamus Tinctorius Oleosomes, Polyhydroxystearic Acid, Aloe (Aloe Barbadensis) Leaf Juice, Knotweed (Polygonum Aviculare) Extract, Tocopheryl Acetate, Perilla (Perilla Frutescens) Extract, Grape (Vitis Vinifera) Fruit Cell Extract, Garden Cress (Lepidium Sativum) Sprout Extract, Squalane, Cetearyl Alcohol, Isononyl Isononanoate, Coco-Glucoside, Pentylene Glycol, Behenyl Alcohol, Xanthan Gum, Triethoxycaprylylsilane, Arachidyl Glucoside, Jojoba (Simmondsia Chinensis) Seed Oil, Stearic Acid, Sucrose Stearate, Phenethyl Alcohol, Tetrahexyldecyl Ascorbate, Glyceryl Caprylate, Ethylene/Propylene/Styrene Copolymer, Sorbitan Oleate, Polyglyceryl-2 Caprate, Propanediol, Alumina, Arachidyl Alcohol, Iron Oxides (CI 77492, CI 77491, CI 77499)

Other Information

Protect this product from excessive heat and direct sunlight

Questions or Comments?

Questions? 1-888-256-8265 or visit www.naplessoap.com

Distributed by: Naples Soap Company • Naples, FL 33913

PRINCIPAL DISPLAY PANEL - 60 mL Bottle Label

NAPLES
SOAP COMPANY

NATURALLY BETTER
SKIN CARE

SUNSCREEN

Broad Spectrum SPF 30

30

Tinted Mineral
Face Cream

2 ﬂ oz (60mL)

TINTED